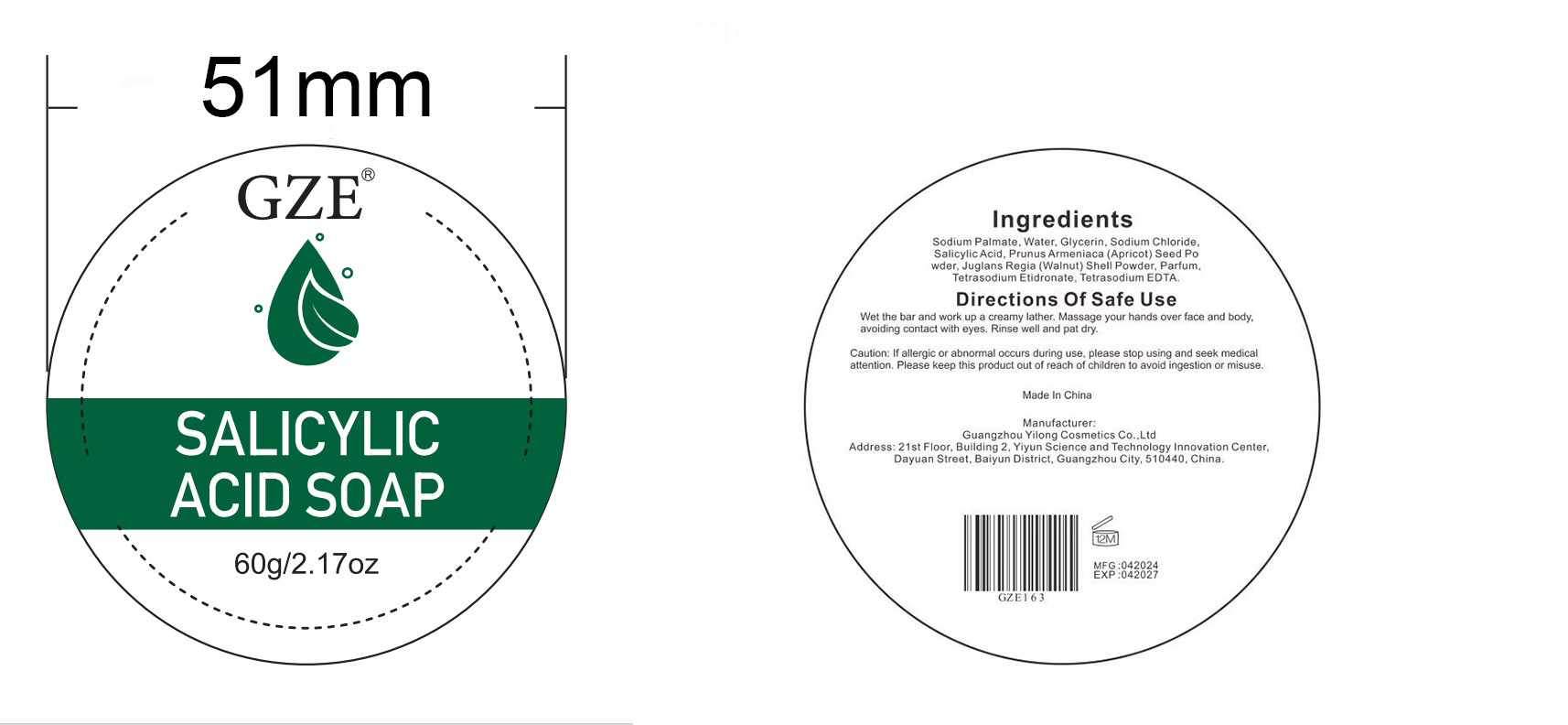 DRUG LABEL: GZE Salicylic AcidSoap
NDC: 74458-163 | Form: SOAP
Manufacturer: Guangzhou Yilong Cosmetics Co., Ltd
Category: otc | Type: HUMAN OTC DRUG LABEL
Date: 20241015

ACTIVE INGREDIENTS: SALICYLIC ACID 2 g/100 g
INACTIVE INGREDIENTS: EDETATE SODIUM; WATER; ETIDRONATE TETRASODIUM; PRUNUS ARMENIACA SEED; JUGLANS REGIA SHELL; SODIUM CHLORIDE; PARFUMIDINE; SODIUM PALMATE; GLYCERIN

GZE SALICYLIC ACID SOAP

INACTIVE INGREDIENT

Sodium Palmate

Water

Glycerin

Sodium Chloride

Prunus Armeniaca (Apricot) Seed Powder

Juglans Regia (Walnut) Shell Powder

Parfum

Tetrasodium Etidronate

Tetrasodium EDTA

ACTIVE INGREDIENT

Salicylic Acid 2%

PURPOSE

Cleanses and exfoliates the skin.

INDICATIONS AND USAGE

Wet the bar and work up a creamy lather. Massage your hands over face and body，avoiding contact with eyes. Rinse well and pat dry.

WARNINGS

For external use only.

Stop use and ask a doctor if rash occurs.

Do not use on damaged or broken skin.

When using this product keep out of eyes. Rinse with water to remove.

Keep out of reach of children. If swallowed, get medical help or contact a Poison Control Center right away.

DOSAGE AND ADMINISTRATION

Wet the bar and work up a creamy lather. Massage your hands over face and body,avoiding contact with eyes. Rinse well and pat dry.